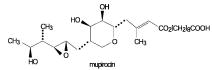 DRUG LABEL: Unknown
Manufacturer: OrthoNeutrogena, Division of Ortho-McNeil Pharmaceutical, Inc.
Category: prescription | Type: HUMAN PRESCRIPTION DRUG LABELING
Date: 20070213

CENTANY™
(mupirocin ointment),2%

OrthoNeutrogena

Rx only For Dermatologic Use

DESCRIPTION

Each gram of Centany (mupirocin ointment),2% contains 20 mg mupirocin in a soft white ointment base consisting of castor oil, oleyl alcohol, hard fat (Softisan® 378) and propylene glycol monostearate. Mupirocin is a naturally occurring antibiotic. The chemical name is (E)-(2S,3R,4R,5S)-5-[(2S,3S,4S,5S)-2,3-Epoxy-5-hydroxy-4-methylhexyl]tetrahydro-3,4-dihydroxy-β-methyl-2 H-pyran-2-crotonic acid, ester with 9-hydroxynonanoic acid. The molecular formula of mupirocin is C26H44O9 and the molecular weight is 500.63. The chemical structure is:

CLINICAL PHARMACOLOGY

Following the application of Centany (mupirocin ointment),2% to a 400 cm^2 area on the back of 23 healthy volunteers once daily for 7 days, the mean (range) cumulative urinary excretion of monic acid over 24 hrs following the last administration was 1.25% (0.2% to 3.0%) of the administered dose of mupirocin. The monic acid concentration in urine collected at specified intervals for 24 hrs on Day 7 ranged from <0.050 to 0.637 μg/mL.

Microbiology: Mupirocin is an antibacterial agent produced by fermentation using the organism Pseudomonas fluorescens. Its spectrum of activity includes gram-positive bacteria. It is also active, in vitro only, against certain gram-negative bacteria. Mupirocin inhibits bacterial protein synthesis by reversibly and specifically binding to bacterial isoleucyl transfer-RNA synthetase. Due to this unique mode of action, mupirocin does not demonstrate cross-resistance with other classes of antimicrobial agents.

When mupirocin resistance occurs, it results from the production of a modified isoleucyl-tRNA synthetase or the acquisition, by genetic transfer, of a plasmid mediating a new isoleucyl-tRNA synthetase. High-level plasmid-mediated resistance (MIC > 500 mcg/mL) has been reported in increasing numbers of isolates of Staphylococcus aureus and with higher frequency in coagulase-negative staphylococci. Methicillin resistance and mupirocin resistance commonly occur together in Staphylococcus aureus and coagulase negative staphylococci.

Mupirocin is bactericidal at concentrations achieved by topical administration. However, the minimum bactericidal concentration (MBC) against relevant pathogens is generally eight-fold to thirty-fold higher than the minimum inhibitory concentration (MIC). In addition, mupirocin is highly protein bound (>97%), and the effect of wound secretions on the MICs of mupirocin has not been determined.

Mupirocin has been shown to be active against susceptible strains of Staphylococcus aureus and Streptococcus pyogenes, both in vitro and in clinical studies. (See INDICATIONS AND USAGE.)

INDICATIONS AND USAGE

Centany (mupirocin ointment),2% is indicated for the topical treatment of impetigo due to: Staphylococcus aureus and Streptococcus pyogenes.

CONTRAINDICATIONS

This drug is contraindicated in individuals with a history of sensitivity reactions to any of its components.

WARNINGS

Centany (mupirocin ointment),2% is not for ophthalmic use.

PRECAUTIONS

If a reaction suggesting sensitivity or chemical irritation should occur with the use of Centany (mupirocin ointment),2%, treatment should be discontinued and appropriate alternative therapy for the infection instituted.

As with other antibacterial products, prolonged use may result in overgrowth of nonsusceptible organisms, including fungi. Centany (mupirocin ointment),2% is not formulated for use on mucosal surfaces. Centany (mupirocin ointment),2% is not intended for nasal use.

PATIENT COUNSELING INFORMATION

Information for Patients: Use this medication only as directed by your healthcare provider. It is for external use only. Avoid contact with the eyes. The medication should be stopped and your healthcare practitioner contacted if irritation, severe itching or rash occurs. If impetigo has not improved in 3 to 5 days, contact your healthcare practitioner.

DRUG INTERACTIONS

Drug Interactions: The effect of the concurrent application of Centany (mupirocin ointment),2% and other drug products is unknown.

CARCINOGENESIS AND MUTAGENESIS AND IMPAIRMENT OF FERTILITY

Carcinogenesis, Mutagenesis, Impairment of Fertility: Long-term studies in animals to evaluate carcinogenic potential of mupirocin have not been conducted.

Results of the following studies performed with mupirocin calcium or mupirocin sodium in vitro and in vivo did not indicate a potential for genotoxicity: rat primary hepatocyte unscheduled DNA synthesis, sediment analysis for DNA strand breaks, Salmonella reversion test (Ames), Escherichia coli mutation assay, metaphase analysis of human lymphocytes, mouse lymphoma assay, and bone marrow micronuclei assay in mice.

Reproduction studies were performed in male and female rats with mupirocin administered subcutaneously at doses up to 14 times the human topical dose (approximately 60 mg mupirocin/ day) on a mg/m^2 basis and revealed neither evidence of impaired fertility nor impaired reproductive performance attributable to mupirocin.

Pregnancy

Teratogenic Effects.

Pregnancy Category B: Reproduction studies have been performed in rats and rabbits with mupirocin administered subcutaneously at doses up to 22 and 43 times, respectively, the human topical dose (approximately 60 mg mupirocin per day) on a mg/m^2 basis and revealed no evidence of harm to the fetus due to mupirocin. There are, however, no adequate and well-controlled studies in pregnant women. Because animal studies are not always predictive of human response, this drug should be used during pregnancy only if clearly needed.

NURSING MOTHERS

Nursing Mothers: It is not known whether this drug is excreted in human milk. Because many drugs are excreted in human milk, caution should be exercised when Centany (mupirocin ointment),2% is administered to a nursing woman.

PEDIATRIC USE

Pediatric Use: The safety and effectiveness of Centany (mupirocin ointment),2% have been established in the age range of 2 months to 16 years. Use of Centany (mupirocin ointment),2% in these age groups is supported by evidence from adequate and well-controlled studies of Centany (mupirocin ointment),2% in impetigo in pediatric patients studied as a part of the pivotal clinical trials. (See CLINICAL STUDIES.)

ADVERSE REACTIONS

The following local adverse reactions have been reported in connection with the use of Centany (mupirocin ointment),2%; application site reactions and pruritus, each in 1% of patients; contact dermatitis and furunculosis, each in 0.7% of patients; and exfoliative dermatitis and rash, each in 0.3% of patients.

DOSAGE AND ADMINISTRATION

A small amount of Centany (mupirocin ointment),2% should be applied to the affected area three times daily. The area treated may be covered with a gauze dressing if desired. Patients not showing a clinical response within 3 to 5 days should be re-evaluated.

CLINICAL STUDIES

The efficacy of topical Centany (mupirocin ointment),2% in impetigo was tested in one study. Patients with impetigo were randomized to receive either Centany (mupirocin ointment), 2% or Bactroban® Ointment (mupirocin ointment, 2%) t.i.d. for 7 days. Clinical efficacy rates at the follow-up visit (one week after end of therapy) in the evaluable populations (adults and pediatric patients included) were 94% for Centany (mupirocin ointment), 2% (n=233) and 95% for Bactroban® Ointment (mupirocin ointment, 2%) (n=242). Pathogen eradication rates at follow-up for both medications were 98%.

Pediatrics

There were 413 pediatric patients aged 2 months to 15 years in the clinical study described above. Clinical efficacy rates at follow-up in the evaluable populations were 93% for Centany (mupirocin ointment), 2% (n=199) and 95% for Bactroban® Ointment (mupirocin ointment, 2%) (n=214).

HOW SUPPLIED

Centany (mupirocin ointment),2% is supplied in 15 gram (NDC 0062-1610-01) and 30 gram (NDC 0062-1610-03) tubes.

Store at controlled room temperature 20° to 25°C (68° to 77°F).

OrthoNeutrogena

Distributed by: OrthoNeutrogena, Division of Ortho-McNeil Pharmaceutical, Inc.
Skillman, New Jersey 08558
©OMP 2004
Rev: April 2004
Printed in USA
635-10-686-3
U.S. Patent No. 6,013,657